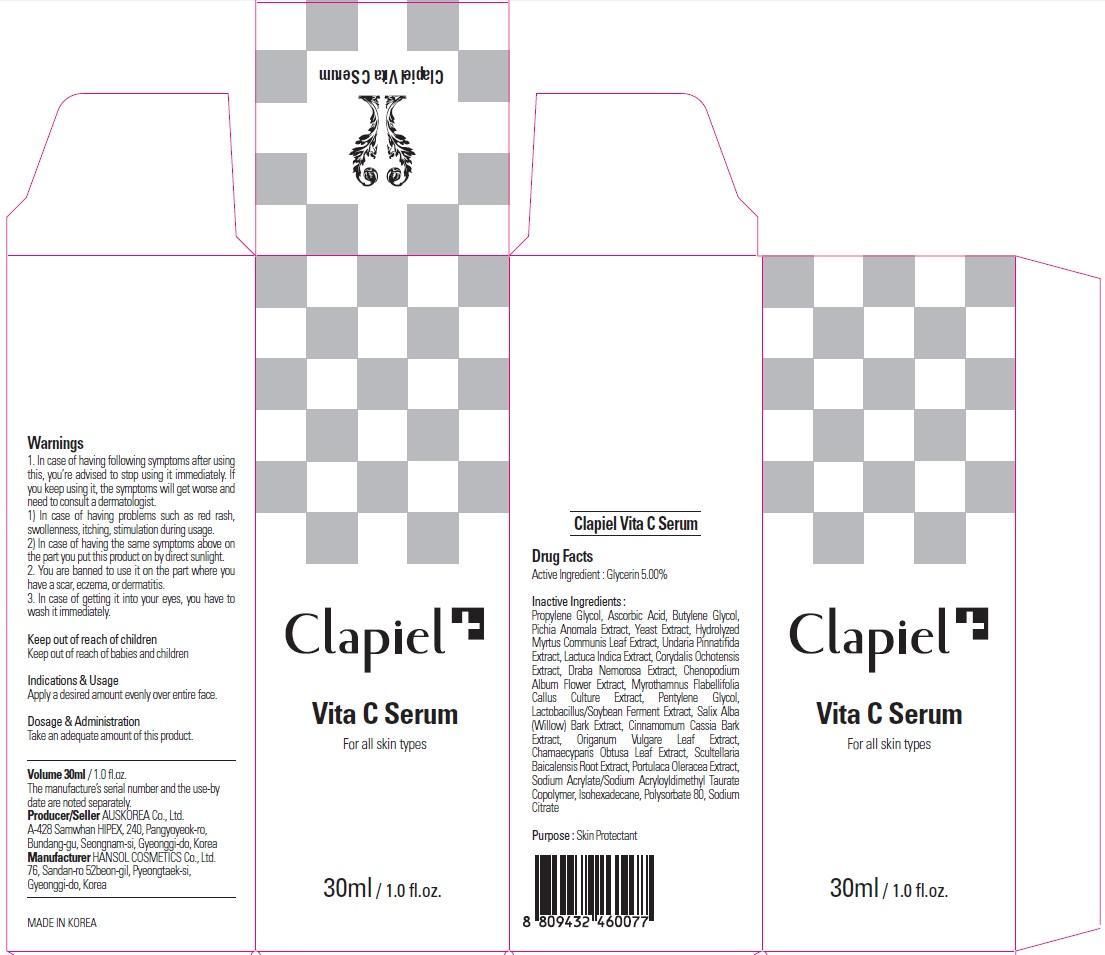 DRUG LABEL: Clapiel Vita C Serum
NDC: 69977-060 | Form: CREAM
Manufacturer: AUS KOREA CO., LTD.
Category: otc | Type: HUMAN OTC DRUG LABEL
Date: 20150724

ACTIVE INGREDIENTS: Glycerin 1.5 mg/30 mL
INACTIVE INGREDIENTS: Propylene Glycol; Ascorbic Acid

ACTIVE INGREDIENT

Active Ingredient: Glycerin 5.00%

INACTIVE INGREDIENT

Inactive Ingredients: Propylene Glycol, Ascorbic Acid, Butylene Glycol, Pichia Anomala Extract, Yeast Extract, Hydrolyzed Myrtus Communis Leaf Extract, Undaria Pinnatifida Extract, Lactuca Indica Extract, Corydalis Ochotensis Extract, Draba Nemorosa Extract, Chenopodium Album Flower Extract, Myrothamnus Flabellifolia Callus Culture Extract, Pentylene Glycol, Lactobacillus/Soybean Ferment Extract, Salix Alba (Willow) Bark Extract, Cinnamomum Cassia Bark Extract, Origanum Vulgare Leaf Extract, Chamaecyparis Obtusa Leaf Extract, Scultellaria Baicalensis Root Extract, Portulaca Oleracea Extract, Sodium Acrylate/Sodium Acryloyldimethyl Taurate Copolymer, Isohexadecane, Polysorbate 80, Sodium Citrate Purpose: Skin Protectant

PURPOSE

Purpose: Skin Protectant

WARNINGS

Warnings: 1. In case of having following symptoms after using this, you’re advised to stop using it immediately. If you keep using it, the symptoms will get worse and need to consult a dermatologist. 1) In case of having problems such as red rash, swollenness, itching, stimulation during usage. 2) In case of having the same symptoms above on the part you put this product on by direct sunlight. 2. You are banned to use it on the part where you have a scar, eczema, or dermatitis. 3. In case of getting it into your eyes, you have to wash it immediately.

KEEP OUT OF REACH OF CHILDREN

Keep out of reach of babies and children

INDICATIONS & USAGE

Indications & Usage: Apply a desired amount evenly over entire face.

DOSAGE & ADMINISTRATION

Dosage & Administration: Take an adequate amount of this product.